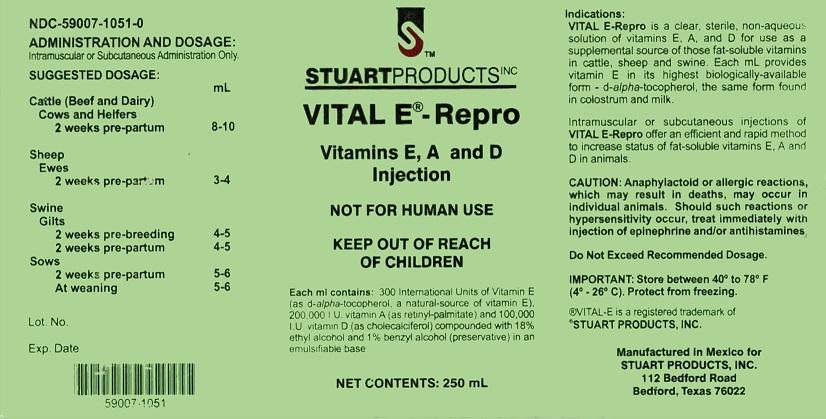 DRUG LABEL: Vital E -
NDC: 59007-1051 | Form: INJECTION, EMULSION
Manufacturer: Stuart Products, Inc.
Category: animal | Type: OTC ANIMAL DRUG LABEL
Date: 20151014

ACTIVE INGREDIENTS: ALPHA-TOCOPHEROL, D- 300 [iU]/1 mL; VITAMIN A PALMITATE 200000 [iU]/1 mL; CHOLECALCIFEROL 100000 [iU]/1 mL
INACTIVE INGREDIENTS: ALCOHOL 180 1/1 mL; BENZYL ALCOHOL 10 1/1 mL

INDICATIONS:

VITAL E–Repro is a clear, sterile, non-aqueous solution of vitamins E, A, and D for use as a supplemental source of those fat-soluble vitamins in cattle, sheep, and swine. Each mL provides vitamin E in its highest biologically-available form - d-alpha-tocopherol, the same form found in colostrum and milk.

Intramuscular or subcutaneous injections of VITAL E-Repro offer an efficient and rapid method to increase status of the fat-soluble vitamins E, A, and D in animals.

ADMINISTRATION AND DOSAGE:

Intramuscular or Subcutaneous Administration Only.

SUGGESTED DOSAGE:

CATTLE (Dairy and Beef)

Cows and Heifers

2 weeks pre-partum 8-10 mL

SHEEP

Ewes

2 weeks pre-partum 3-4 mL

SWINE

Gilts

2 weeks pre-breeding 4-5 mL

2 weeks pre-partum 4-5 mL

Sows

2 weeks pre-partum 5-6 mL

At weaning 5-6 mL

PRECAUTIONS

CAUTION: Anaphylactoid or allergic reactions, which may result in deaths, may occur in individual animals. Should such reactions or hypersensitivity occur, treat immediately with injection of epinephrine and/or antihistamines.

Do Not Exceed Recommended Dosage.

STORAGE AND HANDLING

IMPORTANT: Stored between 40° to 78° F (4°-26°C). Protect from freezing.

®VITAL-E is a registered trademark of

STUART PRODUCTS, INC.

Manufactured in Mexico for

STUART PRODUCTS, INC.

112 Bedford Road

Bedford, Texas 76022

Principal Display Panel - 250 mL Bottle

STUART PRODUCTS INC

VITAL E® - Repro

Vitamin E, A and D Injection

NOT FOR HUMAN USE

KEEP OUT OF REACH OF CHILDREN

Each ml contains: 300 I.U. vitamin E (as d-alpha-tocopherol, a natural-source of vitamin E), 200,000 I.U. Vitamin A (as retinyl-palmitate), and 100,000 I.U. Vitamin D (as cholecalciferl) compounded with 18% ethyl alcohol and 1% benzyl alcohol (preservative) in an emulsifiable base.

NET CONTENTS: 250 mL